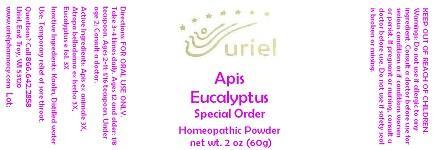 DRUG LABEL: Apis Eucalyptus Special Order
NDC: 48951-1052 | Form: POWDER
Manufacturer: Uriel Pharmacy Inc.
Category: homeopathic | Type: HUMAN OTC DRUG LABEL
Date: 20141117

ACTIVE INGREDIENTS: APIS MELLIFERA 3 [hp_X]/1 g; ATROPA BELLADONNA 3 [hp_X]/1 g; EUCALYPTUS GUM 3 [hp_X]/1 g
INACTIVE INGREDIENTS: KAOLIN; WATER

Apis Eucalyptus Special Order

INDICATIONS AND USAGE

Directions: FOR ORAL USE ONLY.

DOSAGE AND ADMINISTRATION

Take 3-4 times daily. Ages 12 and older: 1/8 teaspoon. Ages 2-11: 1/16 teaspoon. Under age 2: Consult a doctor.

ACTIVE INGREDIENT

Active Ingredients: Apis ex animale 3X, Atropa belladonna ex herba 3X, Eucalyptus e fol. 3X

Inactive Ingredients: Kaolin, Distilled water

PURPOSE

Use: Temporary relief of sore throat.

KEEP OUT OF REACH OF CHILDREN.

WARNINGS

Warnings: Do not use if allergic to any ingredient. Consult a doctor before use for serious conditions or if conditions worsen or persist. If pregnant or nursing, consult a doctor before use. Do not use if safety seal is broken or missing.

QUESTIONS

Questions? Call 866.642.2858 Uriel, East Troy, WI 53120 www.urielpharmacy.com